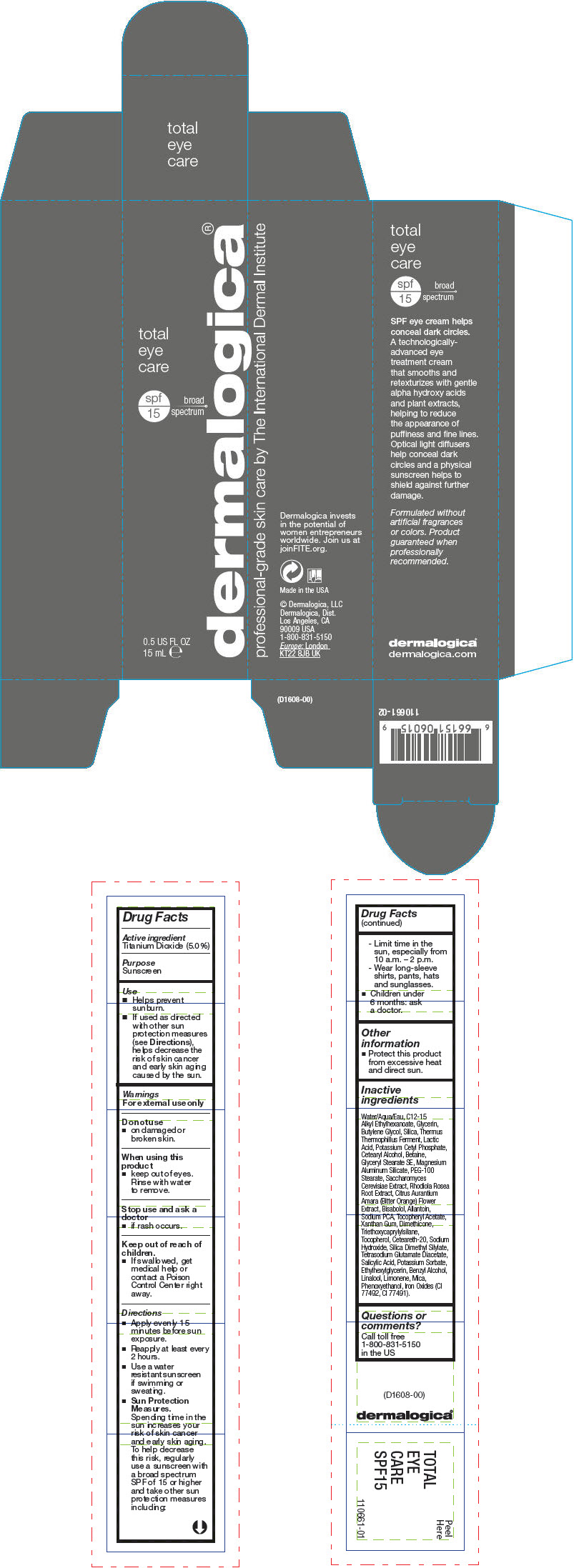 DRUG LABEL: Total Eye Care
NDC: 68479-608 | Form: LOTION
Manufacturer: Dermalogica, Inc.
Category: otc | Type: HUMAN OTC DRUG LABEL
Date: 20171229

ACTIVE INGREDIENTS: Titanium Dioxide 50 mg/1 mL
INACTIVE INGREDIENTS: Water; C12-15 Alkyl Ethylhexanoate; Glycerin; Butylene Glycol; SILICON DIOXIDE; THERMUS THERMOPHILUS LYSATE; LACTIC ACID, UNSPECIFIED FORM; Potassium Cetyl Phosphate; CETOSTEARYL ALCOHOL; Betaine; Glyceryl Stearate SE; Magnesium Aluminum Silicate; PEG-100 Stearate; SACCHAROMYCES CEREVISIAE; SEDUM ROSEUM ROOT; LEVOMENOL; Allantoin; SODIUM PYRROLIDONE CARBOXYLATE; .ALPHA.-TOCOPHEROL ACETATE; Xanthan Gum; Dimethicone; Triethoxycaprylylsilane; Tocopherol; POLYOXYL 20 CETOSTEARYL ETHER; Sodium Hydroxide; Silica Dimethyl Silylate; Tetrasodium Glutamate Diacetate; Salicylic Acid; Potassium Sorbate; Ethylhexylglycerin; LINALOOL, (+/-)-; LIMONENE, (+)-; Mica; Phenoxyethanol; FERROUS OXIDE

Total Eye Care

Drug Facts

Active ingredient

Titanium Dioxide (5.0%)

Purpose

Sunscreen

Use

- Helps prevent sunburn.
- If used as directed with other sun protection measures (see Directions), helps decrease the risk of skin cancer and early skin aging caused by the sun.

Warnings

For external use only

Do not use

- on damaged or broken skin.

When using this product

- keep out of eyes. Rinse with water to remove.

Stop use and ask a doctor

- if rash occurs.

Keep out of reach of children.

- If swallowed, get medical help or contact a Poison Control Center right away.

Directions

- Apply evenly 15 minutes before sun exposure.
- Reapply at least every 2 hours.
- Use a water resistant sunscreen if swimming or sweating.
- Sun Protection Measures.
  Spending time in the sun increases your risk of skin cancer and early skin aging. To help decrease this risk, regularly use a sunscreen with a broad spectrum SPF of 15 or higher and take other sun protection measures including:
  - Limit time in the sun, especially from 10 a.m. – 2 p.m.
  - Wear long-sleeve shirts, pants, hats and sunglasses.
- Children under 6 months: ask a doctor.

Other information

- Protect this product from excessive heat and direct sun.

Inactive ingredients

Water/Aqua/Eau, C12-15 Alkyl Ethylhexanoate, Glycerin, Butylene Glycol, Silica, Thermus Thermophillus Ferment, Lactic Acid, Potassium Cetyl Phosphate, Cetearyl Alcohol, Betaine, Glyceryl Stearate SE, Magnesium Aluminum Silicate, PEG-100 Stearate, Saccharomyces Cerevisiae Extract, Rhodiola Rosea Root Extract, Citrus Aurantium Amara (Bitter Orange) Flower Extract, Bisabolol, Allantoin, Sodium PCA, Tocopheryl Acetate, Xanthan Gum, Dimethicone, Triethoxycaprylylsilane, Tocopherol, Ceteareth-20, Sodium Hydroxide, Silica Dimethyl Silylate, Tetrasodium Glutamate Diacetate, Salicylic Acid, Potassium Sorbate, Ethylhexylglycerin, Benzyl Alcohol, Linalool, Limonene, Mica, Phenoxyethanol, Iron Oxides (CI 77492, CI 77491).

Questions or comments?

Call toll free 1-800-831-5150 in the US

PRINCIPAL DISPLAY PANEL - 15 mL Tube Carton

total
eye
care

spf
15
broad
spectrum

dermalogica®

0.5 US FL OZ
15 mL e